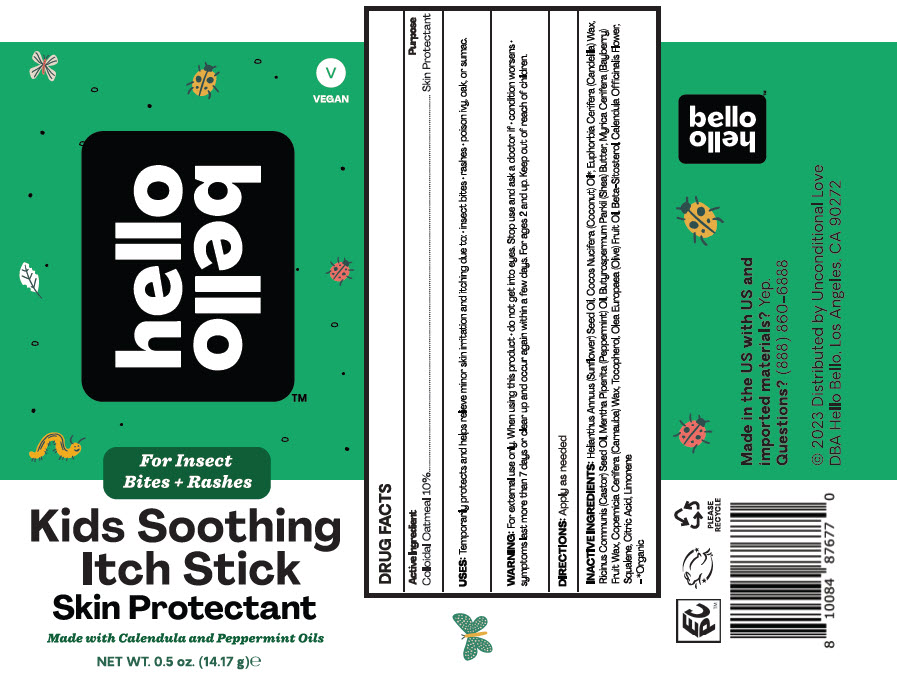 DRUG LABEL: hello bello Kids Soothing Itch Skin Protectant
NDC: 66163-1006 | Form: STICK
Manufacturer: Cosmetic Solutions LLC
Category: otc | Type: HUMAN OTC DRUG LABEL
Date: 20230126

ACTIVE INGREDIENTS: OATMEAL 10 g/100 g
INACTIVE INGREDIENTS: SUNFLOWER OIL; COCONUT OIL; CANDELILLA WAX; CASTOR OIL; PEPPERMINT OIL; SHEA BUTTER; MORELLA CERIFERA FRUIT WAX; CARNAUBA WAX; TOCOPHEROL; OLIVE OIL; .BETA.-SITOSTEROL; CALENDULA OFFICINALIS FLOWER; SQUALENE; CITRIC ACID MONOHYDRATE

hello bello Kids Soothing Itch Stick Skin Protectant

DRUG FACTS

Active Ingredient

Colloidal Oatmeal 10%

Purpose

Skin Protectant

USES

Temporarily protects and helps relieve minor skin irritation and itching due to:

- insect bites
- rashes
- poison ivy, oak, or sumac.

WARNING

For external use only. When using this product

- do not get into eyes.

Stop use and ask a doctor if

- condition worsens
- symptoms last more than 7 days or clear up and occur again within a few days.

For ages 2 and up.

Keep out of reach of children.

DIRECTIONS

Apply as needed

INACTIVE INGREDIENTS

Helianthus Annuus (Sunflower) Seed Oil, Cocos Nucifera (Coconut) Oil [Organic] , Euphorbia Cerifera (Candelilla) Wax, Ricinus Communis (Castor) Seed Oil, Mentha Piperita (Peppermint) Oil, Butyrospermum Parkii (Shea) Butter, Myrica Cerifera (Bayberry) Fruit Wax, Copernicia Cerifera (Carnauba) Wax, Tocopherol, Olea Europaea (Olive) Fruit Oil, Beta-Sitosterol, Calendula Officinalis Flower, Squalene, Citric Acid, Limonene

Questions?

(888) 860-6888

Distributed by Unconditional Love
DBA Hello Bello, Los Angeles, CA 90272

PRINCIPAL DISPLAY PANEL - 14.17 g Stick Label

VEGAN

hello
bello

For Insect
Bites + Rashes

Kids Soothing
Itch Stick
Skin Protectant

Made with Calendula and Peppermint Oils

NET WT. 0.5 oz. (14.17 g)℮